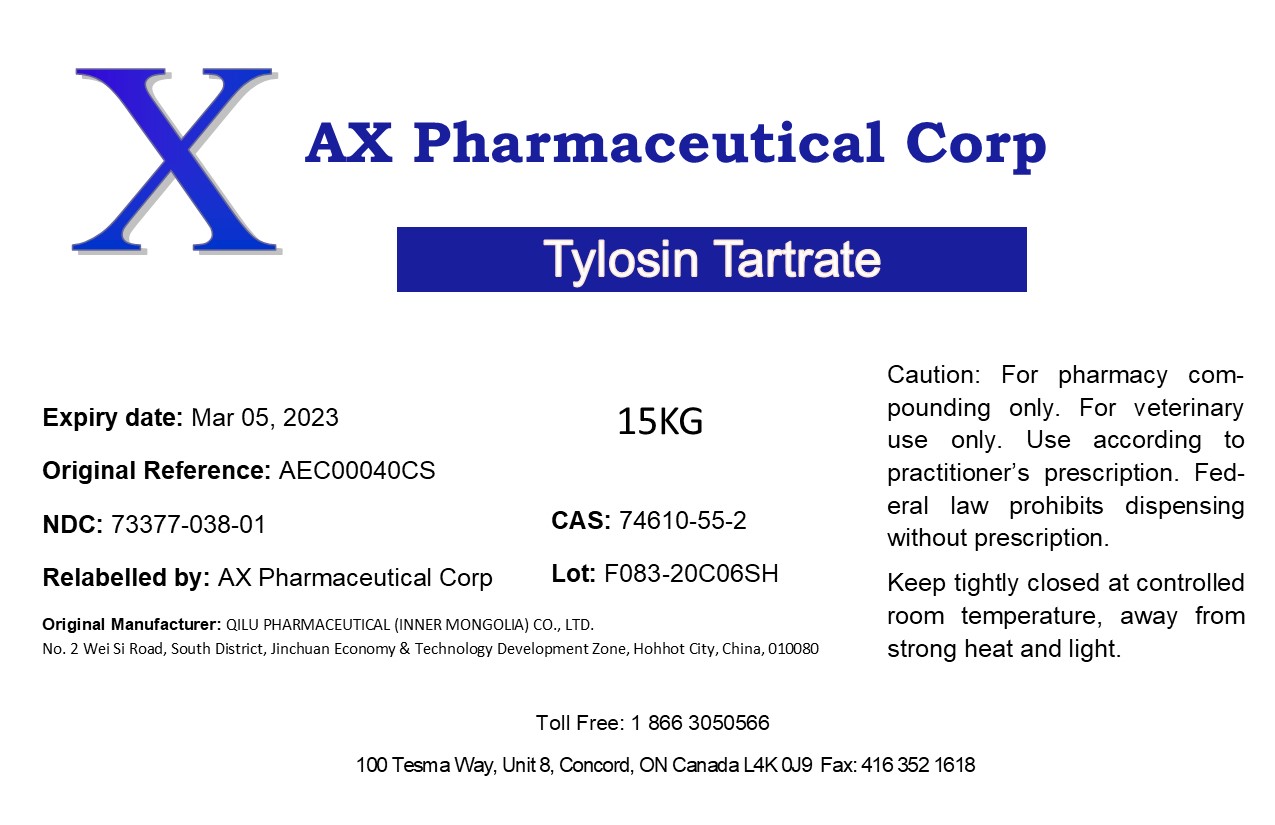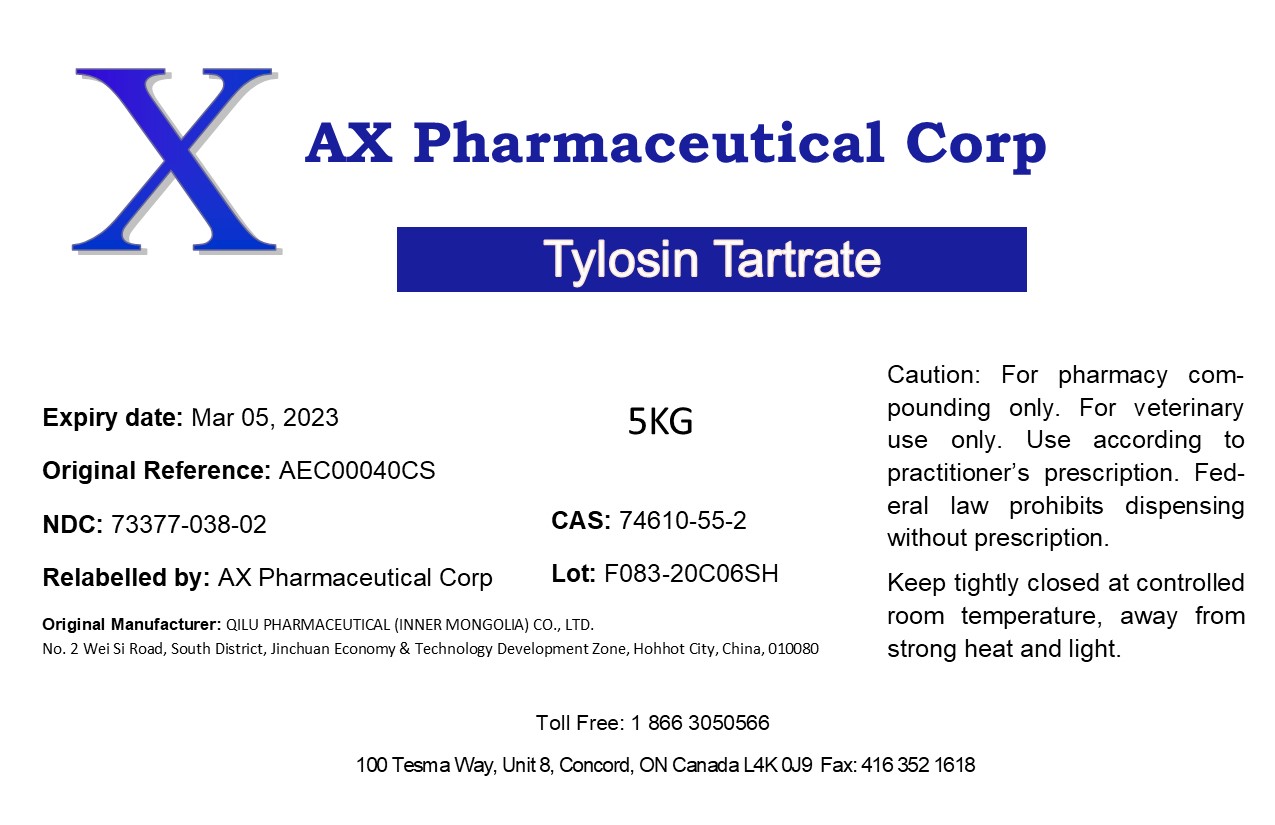 DRUG LABEL: Tylosin Tartrate
NDC: 73377-038 | Form: POWDER
Manufacturer: AX Pharmaceutical Corp
Category: other | Type: BULK INGREDIENT
Date: 20200323

ACTIVE INGREDIENTS: TYLOSIN TARTRATE 1 kg/1 kg

Tylosin Tartrate